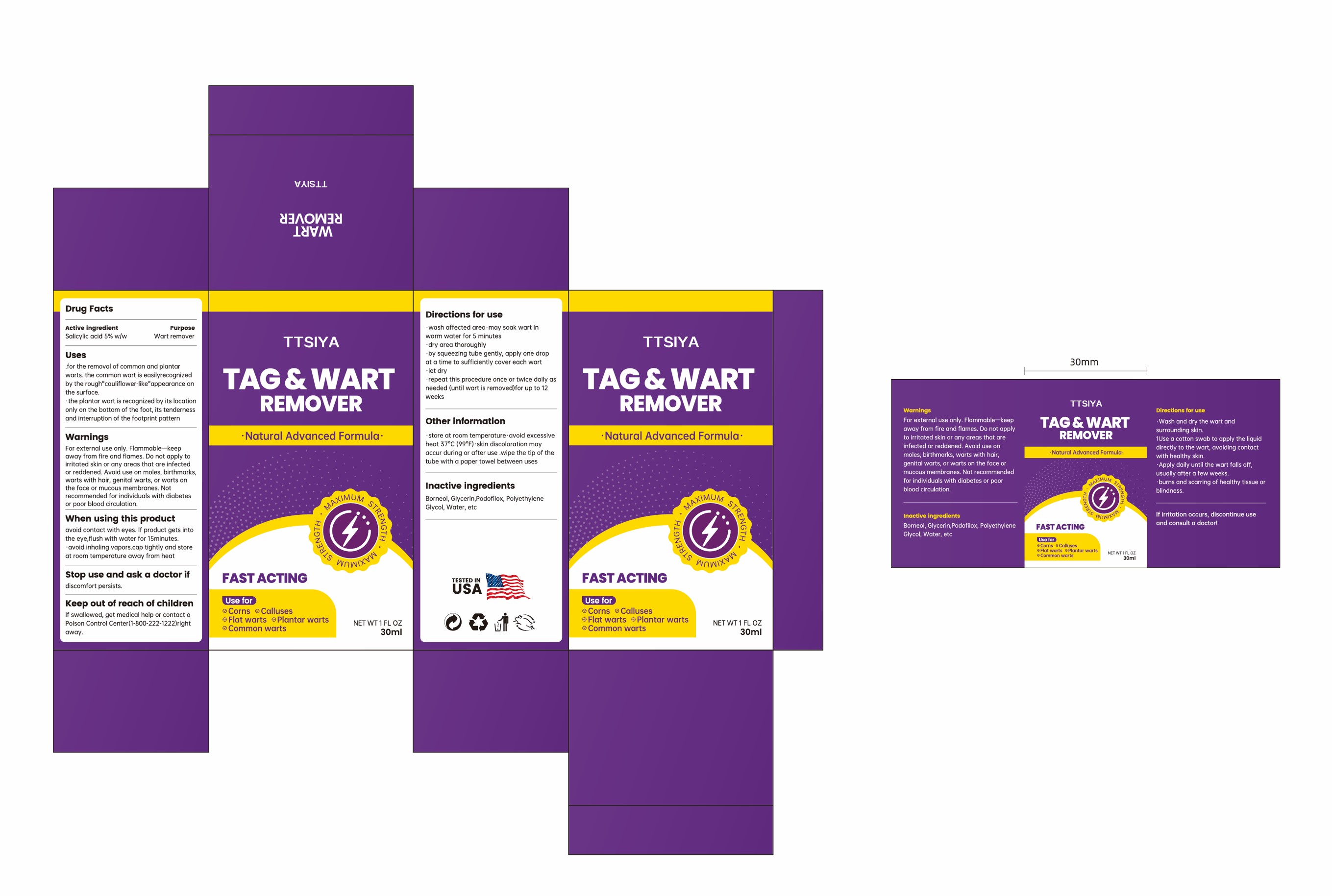 DRUG LABEL: TTSIYA WART REMOVER
NDC: 84867-010 | Form: LIQUID
Manufacturer: Jiashen International Trade Limited
Category: otc | Type: HUMAN OTC DRUG LABEL
Date: 20250211

ACTIVE INGREDIENTS: SALICYLIC ACID 1.5 g/30 mL
INACTIVE INGREDIENTS: GLYCERIN; PODOFILOX; WATER; POLYETHYLENE GLYCOL, UNSPECIFIED; BORNEOL

Active Ingredient

Salicylic acid 5%

Inactive ingredient

Borneol
Glycerin
Podofilox
Polyethylene Glycol
Water

Purpose

Use for
Corns

Calluses

Flat warts

Plantar warts

Common warts

Warning

Warnings
For external use only.Flammable-keepaway from fire and flames. Do not apply toirritated skin or any areas that are infectedor reddened. Avoid use on moles, birthmarks.warts with hair, genital warts, or warts onthe face or mucous membranes. Notrecommended for individuals with diabetesor poor blood circulation.

Stop use and ask a doctor if discomfort persists.

Do not use

Do not apply toirritated skin or any areas that are infectedor reddened. Avoid use on moles, birthmarks,warts with hair, genital warts, or warts onthe face or mucous membranes. Notrecommended for individuals with diabetesor poor blood circulation

Keep out of reach of children

Keep out of reach of childrenIf swallowed, get medical help or contact aPoison Control Center(1-800-222-1222)rightaway.

Directions for use

.wash affected area·may soak wart inwarm water for 5 minutes

*dry area thoroughly·by squeezing tube gently, apply one dropat a time to sufficiently cover each wart.let dry
*repeat this procedure once or twice daily asneeded (until wart is removed)for up to 12weeks

Dosage

wash affected area·may soak wart inwarm water for 5 minutes

*dry area thoroughly·by squeezing tube gently, apply one dropat a time to sufficiently cover each wart.let dry
*repeat this procedure once or twice daily asneeded (until wart is removed)for up to 12weeks

When using this product

avoid contact with eyes. lf product gets intothe eye,flush with water for 15minutes.·avoid inhaling vapors.cap tightly and storeat room temperature away from heat